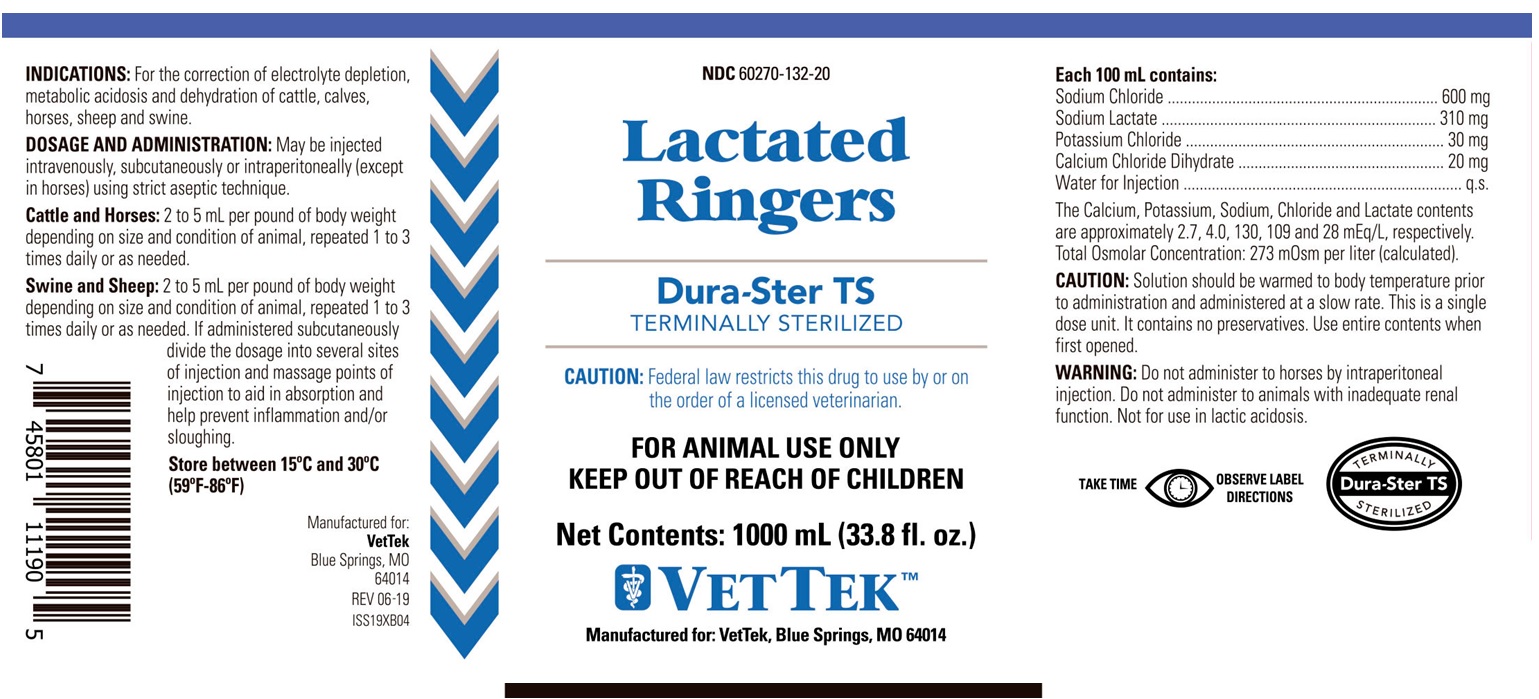 DRUG LABEL: Lactated Ringers
NDC: 60270-132 | Form: INJECTION, SOLUTION
Manufacturer: VetTek
Category: animal | Type: PRESCRIPTION ANIMAL DRUG LABEL
Date: 20191108

ACTIVE INGREDIENTS: SODIUM CHLORIDE 600 mg/100 mL; SODIUM LACTATE 310 mg/100 mL; POTASSIUM CHLORIDE 30 mg/100 mL; CALCIUM CHLORIDE 20 mg/100 mL

LACTATED RINGERS

KEEP OUT OF REACH OF CHILDREN

FOR ANIMAL USE ONLY

CAUTION: Federal law restricts this drug to use by or on the order of a licensed veterinarian.

INDICATIONS:

For the correction of electrolyte depletion, metabolic acidosis and dehydration of cattle, calves, horses, sheep and swine.

DOSAGE AND ADMINISTRATION:

May be injected intravenously, subcutaneously or intraperitoneally (except in horses) using strict aseptic technique.

Cattle and Horses: 2 to 5 mL per pound of body weight depending on size and condition of animal, repeated 1 to 3 times daily or as needed.

Swine and Sheep: 2 to 5 mL per pound of body weight depending on size and condition of animal, repeated 1 to 3 times daily or as needed.

If administered subcutaneously divide the dosage into several sites of injection and massage points of injection to aid in absorption and help prevent inflammation and/or sloughing.

STORAGE AND HANDLING

Store between 15°C and 30°C (59°F-86°F)

INFORMATION FOR OWNERS/CAREGIVERS

Manufactured For
VetTek
Blue Springs, MO
64014

REV 06-19

ISS19XB04

ACTIVE INGREDIENTS

Each 100 mL contains:
Sodium Chloride..................600 mg
Sodium Lactate...................310 mg
Potassium Chloride...............30 mg
Calcium Chloride Dihydrate....20 mg
Water for Injection...................q.s.

The Calcium, Potassium, Sodium, Chloride and Lactate contents are approximately 2.7, 4.0, 130, 109 and 28 mEq/liter, respectively.
Total Osmolar Concentration: 273 mOsm per liter (calculated).

CAUTION:

Solution should be warmed to body temperature prior to administration and administered at a slow rate. This is a single dose unit. It contains no preservatives. Use entire contents when first opened.

WARNING:

Do not administer to horses by intraperitoneal injection. Do not administer to animals with inadequate renal function. Not for use in lactic acidosis.

Principal Display Panel

NDC 60270-132-20

Lactated Ringers

Dura-Ster TS

TERMINALLY STERILIZED

CAUTION: Federal law restricts this drug to use by or on the order of a licensed veterinarian.

KEEP OUT OF REACH OF CHILDREN

FOR ANIMAL USE ONLY

Net Contents: 1000 mL (33.8 fl. oz)

VETTEKTM

Manufactured for: VetTek, Blue Springs, MO 64014